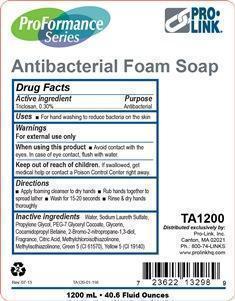 DRUG LABEL: Proformance Antibacterial
NDC: 66908-532 | Form: LIQUID
Manufacturer: Pro-Link, Inc.
Category: otc | Type: HUMAN OTC DRUG LABEL
Date: 20130708

ACTIVE INGREDIENTS: TRICLOSAN 0.30 mg/100 mL
INACTIVE INGREDIENTS: WATER; SODIUM LAURETH SULFATE; PROPYLENE GLYCOL; COCAMIDOPROPYL BETAINE; CITRIC ACID MONOHYDRATE; D&C GREEN NO. 5; FD&C YELLOW NO. 5; PEG-7 GLYCERYL COCOATE; GLYCERIN; METHYLCHLOROISOTHIAZOLINONE; METHYLISOTHIAZOLINONE; BRONOPOL

Drug Facts

Active ingredient

Triclosan, 0.30%

Purpose

Antibacterial

Uses

For hand washing to reduce bacteria on the skin

Warnings

For external use only

When using this product

avoid contact with eyes. In case of eye contact, flush with water.

Keep out of reach of children.

If swallowed, get medical help or contact a Poison Control Center right away.

Directions

Apply foaming cleanser to dry hands

Rub hands together to spread lather

Wash for 15-20 seconds

Rinse and dry hands thoroughly

Inactive ingredients

Water, Sodium Laureth Sulfate, Propylene Glycol, PEG-7 Glyceryl Cocoate, Glycerin, Cocamidopropyl Betaine, 2-Bromo-2-nitropropane-1,3-diol, Fragrance, Citric Acid, Methylchloroisothiazolinone, Methylisothiazolinone, Green 5 (CI 61570), Yellow 5 (CI 19140).

PACKAGE LABEL

ProFormance Series

ProLink

Antibacterial Foam Soap

TA1200

Distributed exclusively By:

Pro-Link, Inc.

Canton, MA 02021

Ph.: 800-74-LINKS

www.

Rev. 07-13

1200 mL

40.6 Fluid Ounces